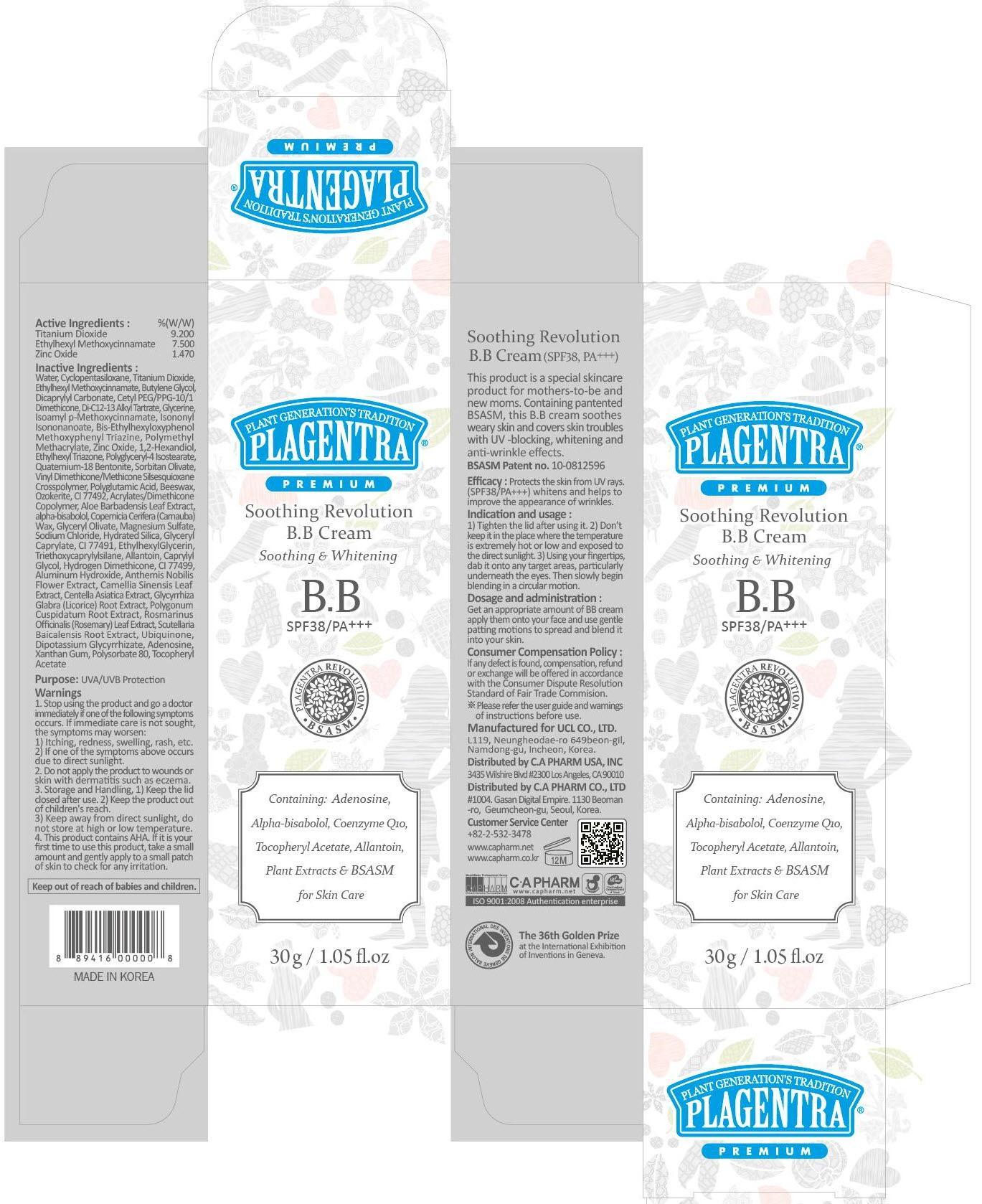 DRUG LABEL: PLAGENTRA SOOTHING REVOLUTION BB
NDC: 68988-110 | Form: CREAM
Manufacturer: C.A Pharm Co., Ltd.
Category: otc | Type: HUMAN OTC DRUG LABEL
Date: 20141205

ACTIVE INGREDIENTS: Titanium Dioxide 2.77 g/30 g; OCTINOXATE 2.25 g/30 g; Zinc Oxide 0.35 g/30 g
INACTIVE INGREDIENTS: Water; Butylene Glycol

ACTIVE INGREDIENT

Active Ingredients: Titanium Dioxide 9.24%, Ethylhexyl Methoxycinnamate 7.5%, Zinc Oxide 1.17%

INACTIVE INGREDIENT

Inactive Ingredients:
Water, Cyclopentasiloxane, Butylene Glycol, Ethylhexyl Triazone, Di-C12-13 Alkyl Tartrate, Cetyl Ethylhexanoate, Dicaprylyl Carbonate, Cetyl PEG/PPG-10/1 Dimethicone, Glycerin, PEG-10 Dimethicone, Vinyl Dimethicone/Methicone Silsesquioxane Crosspolymer, 1,2-Hexanediol, Polyglyceryl-4 Isostearate, Hydrated Silica, Sodium Chloride, Magnesium Sulfate, CI 77492, Quaternium-18 Bentonite, Copernicia Cerifera (Carnauba) Wax, Ozokerite, Hydrogen Dimethicone, Aloe Arborescens Leaf Extract, Bisabolol, Beeswax, Aluminum Hydroxide, Dimethicone Crosspolymer, CI 77491, Polyglutamic Acid, Triethoxycaprylylsilane, CI 77499, Caprylic/Capric Triglyceride, Tocopheryl Acetate, Chamomilla Recutita (Matricaria) Flower/Leaf Extract, Eugenia Caryophyllus (Clove) Flower Extract, Citrus Paradisi (Grapefruit) Fruit Extract, Eucalyptus Globulus Leaf Extract, Citrus Junos Fruit Extract, Sophora Angustifolia Root Extract, Centella Asiatica Extract, Scutellaria Baicalensis Root Extract, Polygonum Cuspidatum Root Extract, Camellia Sinensis Leaf Extract, Glycyrrhiza Glabra (Licorice) Root Extract, Anthemis Nobilis Flower Extract, Rosmarinus Officinalis (Rosemary) Leaf Extract, Polysorbate 80, Allantoin, Dipotassium Glycyrrhizate, Alcohol, Adenosine, Lecithin, Ubiquinone

PURPOSE

Purpose: UVA/UVB Protection

WARNINGS

1. Stop using the product and go to a doctor immediately if one of the following symptoms occurs. If immediate care is not sought, the symptoms may worsen :
1) Itching, redness, swelling, rash, etc. 2) If one of the symptoms above occurs due to direct sunlight.
2. Do not apply the product to wounds or skin with dermatitis such as eczema.
3. Storage and Handling, 1) Keep the lid closed after use. 2) Keep the product out of children's reach. 3) Keep away from direct sunlight, do not store at high or low temperature.
4. It contains AHA. If it is your first time to use this product, take a small amount and gently apply to the skin to check if it cause andy trouble to your skin.

KEEP OUT OF REACH OF CHILDREN

Keep out of reach of babies and children.

INDICATIONS & USAGE

Indication and usage:
1) Tighten the lid after using it.
2) Don't keep it in the place where the temperature is extremely hot or low and exposed to the direct sunlight.
3) Using your fingertips, dab it onto any target areas, particularly underneath the eyes. Then slowly begin blending in a circular motion.

DOSAGE & ADMINISTRATION

Dosage and administration:
Get an appropriate amount of BB cream apply them onto your face and use gentle patting motions to spread and blend it into your skin.